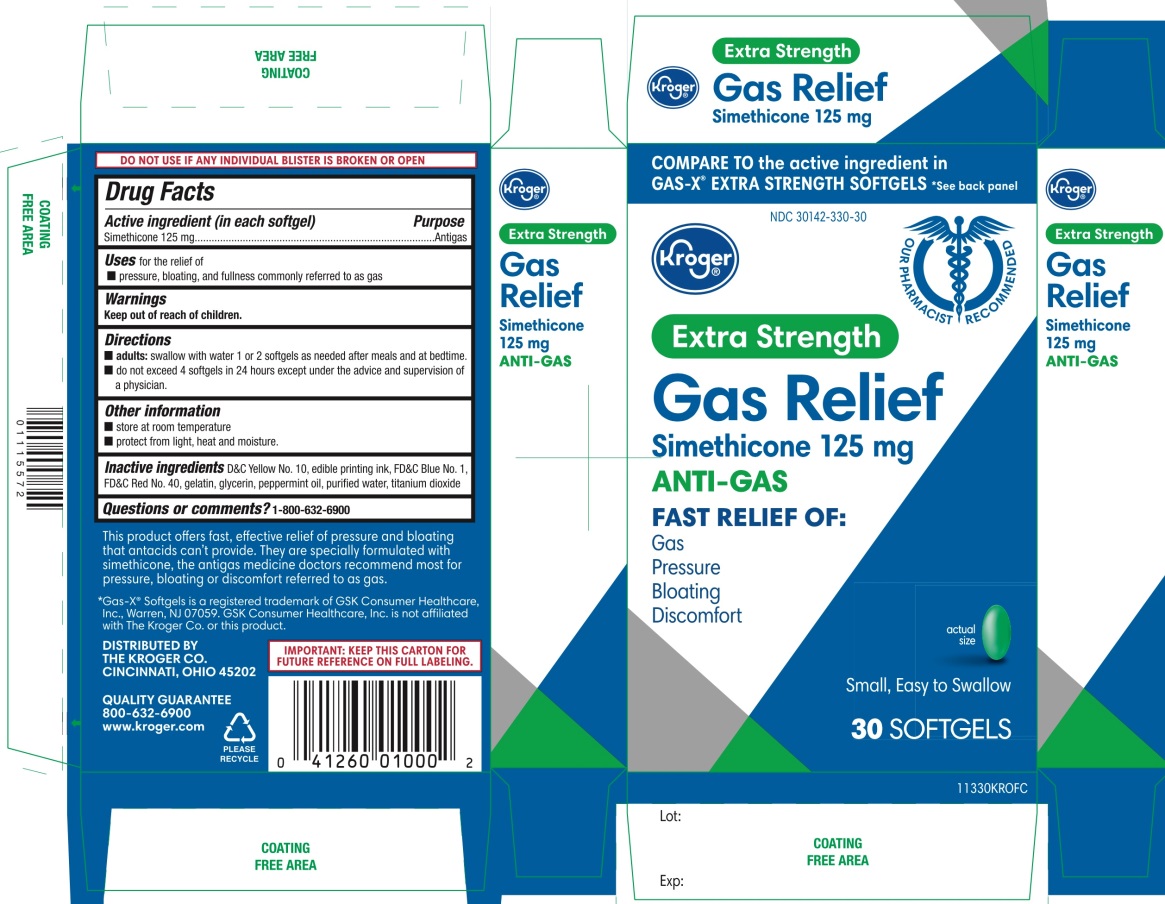 DRUG LABEL: Kroger Extra Strength
NDC: 30142-330 | Form: CAPSULE, LIQUID FILLED
Manufacturer: KROGER COMPANY
Category: otc | Type: HUMAN OTC DRUG LABEL
Date: 20250801

ACTIVE INGREDIENTS: DIMETHICONE, UNSPECIFIED 125 mg/1 1
INACTIVE INGREDIENTS: D&C YELLOW NO. 10; FD&C BLUE NO. 1; FD&C RED NO. 40; GELATIN, UNSPECIFIED; GLYCERIN; PEPPERMINT OIL; WATER; TITANIUM DIOXIDE

Kroger Extra Strength Gas Relief 30 Softgels Drug Facts

Active ingredient (in each softgel)

Simethicone 125 mg

Purpose

Antigas

Uses

for relief of:

- pressure, bloating and fullness commonly referred to as gas

Directions

- adults:swallow with water 1 or 2 softgels as needed after meals and at bedtime.
- do not exceed 4 softgels in 24 hours except under the advice and supervision of a physician.

Other information

- store at room temperature
- protect from light, heat and moisture.

Inactive ingredients

D&C Yellow No. 10, edible printing ink, FD&C Blue No. 1, FD&C Red No. 40, gelatin, glycerin, peppermint oil, purified water, titanium dioxide.

Questions or comments?

1-800-632-6900

Principal Display Panel

NDC 30142-330-30

COMPARE TO the active ingredient GAS-X® EXTRA STRENGTH SOFTGELS *See back panel

Extra Strength

Gas Relief

Simethicone/125 mg

ANTI-GAS

FAST RELIEF OF:

- Gas
- Pressure
- Bloating
- Discomfort

Small, Easy to Swallow

30 SOFTGELS

IMPORTANT:KEEP THIS CARTON FOR FUTURE REFERENCE ON FULL LABELING.

This product offers, effective relief of pressure and bloating that antacid can’t provide. They are specially formulated with simethicone, the antigas medicine doctors recommend most for pressure, bloating or discomfort referred to as gas.

*Gas-X® Softgels is registered trademark of GSK Consumer Healthcare, Inc. Warren, NJ 07059. GSK Consumer Healthcare, Inc. is not affiliated with The Kroger Co. or this product.

DO NOT USE IF ANY INDIVIDUAL BLISTERS UNIT IS BROKEN OR OPEN.

DISTRIBUTED BY:

THE KROGER CO.

CINCINNATI, OHIO 45202

QUALITY GUARANTEE

800-632-6900

www.kroger.com